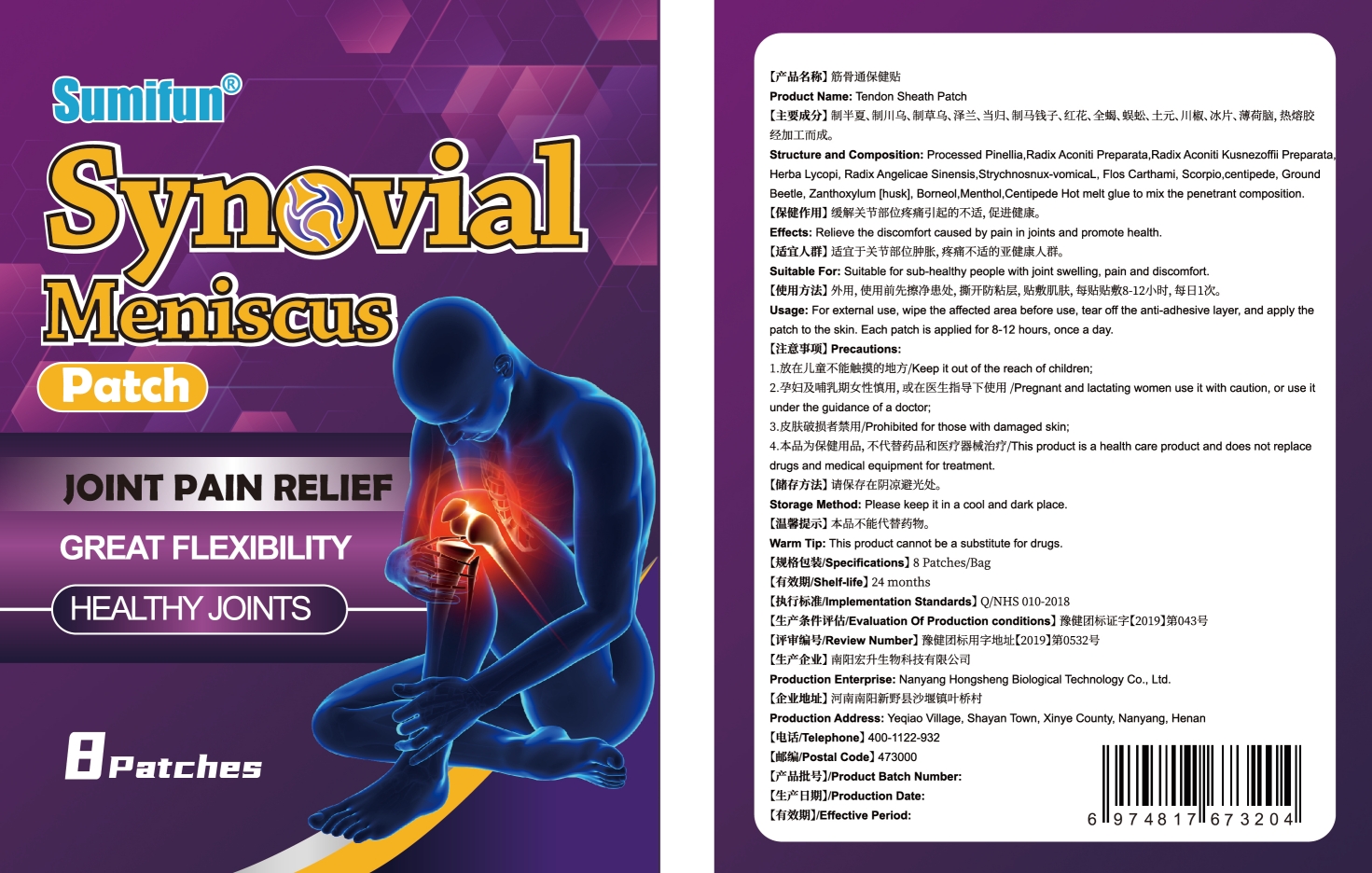 DRUG LABEL: Tendon Sheath Patch
NDC: 83675-006 | Form: PATCH
Manufacturer: Guangzhou Hanhai Trading Co., Ltd
Category: otc | Type: HUMAN OTC DRUG LABEL
Date: 20230920

ACTIVE INGREDIENTS: BORNEOL 15 g/100 1
INACTIVE INGREDIENTS: PINELLIA TERNATA ROOT; ANGELICA BISERRATA WHOLE; EUPOLYPHAGA SINENSIS; SAFFLOWER; MENTHOL; ACONITINE; PROFLURALIN; SCOLOPENDRA SUBSPINIPES; ZANTHOXYLUM FAGARA WHOLE; ANDROCTONUS AUSTRALIS WHOLE

Active Ingredient

Borneol 15.0%

Purpose

Relief Joint Pain

Use

Tendon Sheath Patch to help relief joint pain

Warnings

For external use only. Do not take it internally.

Keep Out Of Reach Of Children
Prohibited for those with damaged skin.

Do not use

Product shall not be eat

When Using

Do not stick around eyes and mouth,This product cannot replace drugs.

Stop Use

In case of adverse reactions, please stop using this product.If the symptoms.

Ask Doctor

ask doctor in case of adverse reactions

Keep Oot Of Reach Of Children

Keep Out Of Reach Of Children

Directions

Take one piece of this product when needed, remove the waxpaper,

stick to the desired area and press the surrounding, replace it every 8-12 hours.

Children should be used under adult supervision.

Other information

Store the product in a cool, dry and well-ventilated place

Avoid direct sunlight

Inactive ingredients

Processed Pinellia,

Radix Aconiti PreparataRadix Aconiti Kusnezoffi PreparaHerba Lycopi,

Radix Angelicae Sinensis,

Flos Carthami,

Scorpio,

centipede.

GroundBeetle,

Zanthoxvlum huskl.

Menthol.

Centipede Hot melt alue